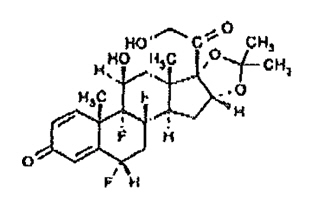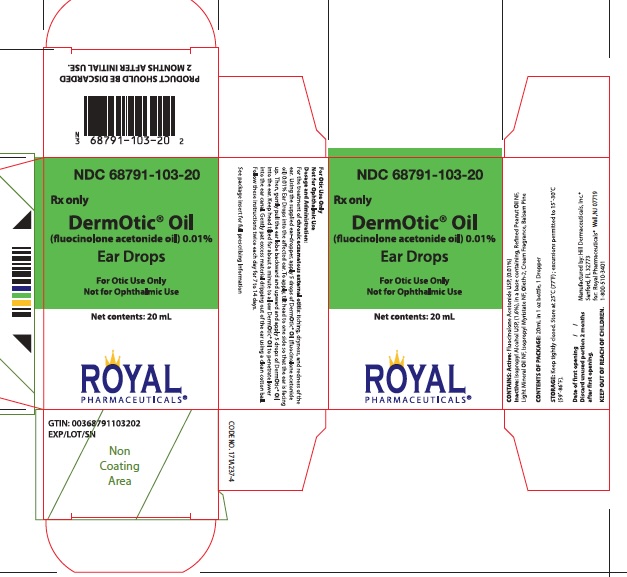 DRUG LABEL: DERMOTIC
NDC: 68791-103 | Form: OIL
Manufacturer: Royal Pharmaceuticals
Category: prescription | Type: HUMAN PRESCRIPTION DRUG LABEL
Date: 20250509

ACTIVE INGREDIENTS: fluocinolone acetonide 0.11 mg/1 mL
INACTIVE INGREDIENTS: ISOPROPYL ALCOHOL; ISOPROPYL MYRISTATE; LIGHT MINERAL OIL; OLETH-2; PEANUT OIL

HIGHLIGHTS OF PRESCRIBING INFORMATION

These highlights do not include all the information needed to use DERMOTIC OIL safely and effectively. See full prescribing information for DERMOTIC OIL.
DERMOTIC OIL (fluocinolone acetonide) ear drops, for otic use
Initial U.S. Approval: 1988

1 INDICATIONS AND USAGE

DERMOTIC® OIL is a corticosteroid indicated for the topical treatment of chronic eczematous external otitis in adults and pediatric patients 2 years of age and older. (1)

2 DOSAGE AND ADMINISTRATION

• DERMOTIC OIL is not for oral, ophthalmic, or intravaginal use. (2)

• Apply 5 drops of DERMOTIC OIL into the affected ear twice daily for 7 to 14 days. (2)

• Do not use on face or intertriginous areas. (2)

3 DOSAGE FORMS AND STRENGTHS

Ear drops, containing 0.01% fluocinolone acetonide, supplied in bottles containing 20 mL. (3)

4 CONTRAINDICATIONS

None. (4)

5 WARNINGS AND PRECAUTIONS

- Endocrine System Adverse Reactions:
  o Topical corticosteroids can produce reversible hypothalamic-pituitary-adrenal (HPA) axis suppression, Cushing’s syndrome, hyperglycemia, and glucosuria. (5.1)
  o Pediatric patients may be more susceptible to systemic toxicity from equivalent doses. (5.1,8.4)
  o Systemic absorption may require evaluation for HPA axis suppression. Potent corticosteroids use on large areas, prolonged use or occlusive use, altered skin barrier, liver failure, and young age may increase systemic absorption. Modify use should HPA axis suppression develop. (5.1).
- Local Adverse Reactions: Local adverse reactions may include atrophy, striae irritation, acneiform eruptions, hypopigmentation, and allergic contact dermatitis, and may be more likely with occlusive use or more potent corticosteroids. (5.2, 6.1)
- Ophthalmic Adverse Reactions: May increase the risks of glaucoma and posterior subcapsular cataract. Avoid contact of DERMOTIC OIL with eyes. Advise patients to report any visual symptoms and consider referral to an ophthalmologist for evaluation. (5.3)

6 ADVERSE REACTIONS

The most commonly reported adverse reactions (≥ 1%) were headache (3%), URI (2%), cough (2%), eczematous otitis (1%). (6.1)
To report SUSPECTED ADVERSE REACTIONS, contact Hill Dermaceuticals, Inc. at 1-800-344-5707 or FDA at 1-800-FDA-1088 or www.fda.gov/medwatch.

FULL PRESCRIBING INFORMATION

1 INDICATIONS AND USAGE

DermOtic® Oil is indicated for the topical treatment of chronic eczematous external otitis in adults and pediatric patients 2 years of age and older.

2 DOSAGE AND ADMINISTRATION

DERMOTIC OIL is for otic administration only. Not for oral, ophthalmic, or intravaginal use.

Apply DERMOTIC OIL into the affected ear using the supplied ear dropper. To apply, tilt head to one side so that the ear is facing up. Then gently pull the ear lobe backward and upward and apply 5 drops of DERMOTIC OIL into the ear. Keep head tilted for about a minute to allow DERMOTIC OIL to penetrate lower into the ear canal. Gently pat excess material dripping out of the ear using a clean cotton ball. Follow these instructions twice each day for 7 to 14 days.

Discontinue DERMOTIC OIL when control of disease is achieved within 2 weeks, or contact the healthcare provider if no improvement is seen within 2 weeks.

Do not use on the face, axillae, or groin unless directed by the healthcare provider. Do not apply to intertriginous areas due to the increased risk of local adverse reactions [see Adverse Reactions (6) and Use in Specific Populations (8.4)].

3 DOSAGE FORMS AND STRENGTHS

Ear drops, containing 0.01% fluocinolone acetonide supplied in bottles containing 20 mL (dropper included).

4 CONTRAINDICATIONS

None.

5 WARNINGS AND PRECAUTIONS

5.1 Endocrine System Adverse Reactions

Systemic absorption of topical corticosteroids can produce reversible hypothalamic-pituitary-adrenal (HPA) axis suppression with the potential for glucocorticosteroid insufficiency. Cushing’s syndrome, hyperglycemia, and glucosuria can result from systemic absorption of topical corticosteroids.

HPA axis suppression and Cushing’s syndrome have been reported in pediatric patients receiving topical corticosteroids. Manifestations of adrenal suppression in pediatric patients include linear growth retardation, delayed weight gain, low plasma cortisol levels, and subnormal response to ACTH stimulation. Pediatric patients may be more susceptible to systemic toxicity from equivalent doses due to their larger skin surface to body mass ratios [see Use in Specific Populations (8.4)].

Conditions which increase systemic absorption include the use of more potent corticosteroids, use over large surface areas, use over prolonged periods, use of occlusive dressings, altered skin barrier, liver failure, and young age. Use of more than one corticosteroid-containing product at the same time may increase total systemic corticosteroid exposure.
Because of the potential for systemic absorption, use of topical corticosteroids may require that patients be periodically evaluated for HPA axis suppression. The ACTH stimulation test may be helpful in evaluating patients for HPA axis suppression.

If HPA axis suppression is documented, an attempt should be made to withdraw the drug to reduce the frequency of application, or to substitute a less potent corticosteroid. Manifestations of adrenal insufficiency may require supplemental systemic corticosteroid. Recovery of HPA axis function is generally prompt upon discontinuation of topical corticosteroids.

5.2 Local Adverse Reactions

Local adverse reactions may occur with use of topical corticosteroids, including DERMOTIC OIL, and may be more likely to occur with occlusive use, prolonged use, or use of higher potency corticosteroids. Some local adverse reactions may be irreversible. Reactions may include atrophy, striae, telangiectasias, burning, itching, irritation, dryness, folliculitis, acneiform eruptions, hypopigmentation, perioral dermatitis, allergic contact dermatitis, secondary infection, and miliaria [see Adverse Reactions (6.1)].

5.3 Ophthalmic Adverse Reactions

Use of topical corticosteroids may increase the risks of glaucoma and posterior subcapsular cataract. Glaucoma and cataracts have been reported in postmarketing experience with the use of topical corticosteroid products. Avoid contact of DERMOTIC OIL with eyes. Advise patients to report any visual symptoms and consider referral to an ophthalmologist for evaluation.

5.4 Allergic Contact Dermatitis

Use of topical corticosteroids can cause allergic contact dermatitis. Allergic contact dermatitis to any component of topical corticosteroids is usually diagnosed by a failure to heal rather than a clinical exacerbation. Clinical diagnosis of allergic contact dermatitis can be confirmed by patch testing.

5.5 Concomitant Skin Infections

Use of topical corticosteroids may delay healing or worsen concomitant skin infections. Treat concomitant skin infections with an appropriate antimicrobial agent. If the infection persists unchanged, discontinue DERMOTIC OIL until the infection has been adequately treated.

5.6 Use in Peanut Sensitive Individuals

Use caution in prescribing DERMOTIC OIL for peanut sensitive individuals [see Description (11)].

Should signs of hypersensitivity present (wheal and flare reactions, pruritus, or other manifestations), or should disease exacerbations occur, discontinue DERMOTIC OIL immediately and institute appropriate therapy.

6 ADVERSE REACTIONS

The following serious adverse reactions are discussed in more detail in other sections of the labeling:
• Endocrine System Adverse Reactions [see Warnings and Precautions (5.1), Use in Specific Populations (8.4)]
• Local Adverse Reactions [see Warnings and Precautions (5.2)]
• Ophthalmic Adverse Reactions [see Warnings and Precautions (5.3)]

6.1 Clinical Studies Experience

Because clinical trials are conducted under widely varying conditions, adverse reaction rates observed in the clinical trials of a drug cannot be directly compared to rates in the clinical trials of another drug and may not reflect the rates observed in practice.

In trials that enrolled 154 subjects (adults and pediatric subjects 2 years and older) with chronic eczematous external otitis who were treated with five drops per ear of DERMOTIC OIL twice daily for a maximum 14 days of treatment, the following adverse reactions were reported:

Table 1: Adverse Reactions in ≥ 1% of DERMOTIC OIL-Treated Adult and Pediatric Subjects 2 Years of Age and Older with Chronic Eczematous External Otitis, N=154
Adverse Reaction | n (%)
Headache | 4 (3)
URI | 3 (2)
Cough | 3 (2)
Eczematous otitis | 2 (1)

6.2 Postmarketing Experience

The following adverse reactions have been identified during post-approval use of products containing topical corticosteroids. Because postmarketing adverse reactions are reported voluntarily from a population of uncertain size, it is not always possible to reliably estimate their frequency or establish a causal relationship to drug exposure.

- Endocrine Disorders: HPA axis suppression and Cushing’s syndrome [see Use in Specific Populations (8.4)]
- Eye Disorders: glaucoma and cataracts [see Warnings and Precautions (5.3)]
- Nervous System Disorders: intracranial hypertension including bulging fontanelles, headaches, and bilateral papilledema [see Use in Specific Populations (8.4)]

8 USE IN SPECIFIC POPULATIONS

8.1 Pregnancy

Risk Summary
Available data from case reports, case series, and observational studies on fluocinolone acetonide use in pregnant women have not identified a drug-associated risk of major birth defects, miscarriage or adverse maternal or fetal outcomes. Observational studies suggest maternal use of high to super-high potency topical steroids may be associated with an increased risk of low birthweight infants. Advise pregnant women to use DERMOTIC OIL on the smallest area of skin and for the shortest duration possible.

Corticosteroids can cause fetal malformations in laboratory animals when administered systemically at relatively low dosage levels. Some corticosteroids cause fetal malformations after dermal application in laboratory animals.

The background risk of major birth defects and miscarriage for the indicated population is unknown. All pregnancies have a background risk of birth defect, loss, or other adverse outcomes. In the U.S. general population, the estimated background risk of major birth defects and miscarriage in clinically recognized pregnancies is 2 to 4% and 15 to 20%, respectively.

8.2 Lactation

Risk Summary
There is no information regarding the presence of fluocinolone acetonide in breast milk or its effects on the breastfed infant or on milk production. It is not known whether topical administration of corticosteroids could result in sufficient systemic absorption to produce detectable quantities in breast milk. The developmental and health benefits of breastfeeding should be considered along with the mother’s clinical need for DERMOTIC OIL and any potential adverse effects on the breastfed infant from DERMOTIC OIL or from the underlying maternal condition.

8.4 Pediatric Use

The safety and effectiveness of DERMOTIC OIL for the topical treatment of chronic eczematous external otitis have been established in pediatric patients aged 2 years and older.

Safety and effectiveness of DERMOTIC OIL in pediatric patients with chronic eczematous external otitis below the age of 2 years have not been established.

Systemic Adverse Reactions in Pediatric Patients
HPA Axis suppression, Cushing’s syndrome, and intracranial hypertension have been reported in pediatric patients receiving topical corticosteroids. Manifestations of adrenal suppression in pediatric patients include linear growth retardation, delayed weight gain, low plasma cortisol levels, and subnormal response to ACTH stimulation. Manifestations of intracranial hypertension include bulging fontanelles, headaches, and bilateral papilledema.
Because of a higher ratio of skin surface area to body mass, pediatric patients are at a greater risk for systemic adverse reactions than are adults when treated with topical corticosteroids [see Warnings and Precautions (5.1)].

Evaluation in Peanut-Sensitive Pediatric Patients
A clinical trial was conducted to assess the safety of the formulation of DERMOTIC OIL, which contains refined peanut oil, in patients with known peanut allergies. The trial enrolled 13 pediatric subjects with atopic dermatitis, 6 to 17 years of age. DERMOTIC OIL is not approved for the treatment of atopic dermatitis. Of the 13 subjects, 9 were Radioallergosorbent Test (RAST) positive to peanuts and 4 had no peanut sensitivity (controls). The trial evaluated the subjects’ responses to both prick test and patch test utilizing refined peanut oil, the formulation of DERMOTIC OIL and histamine/saline controls. Subjects were also treated with the formulation of DERMOTIC OIL twice daily for 7 days. Prick test and patch test results for all 13 subjects were negative to the formulation of DERMOTIC OIL and the refined peanut oil. One of the 9 peanut-sensitive subjects experienced an exacerbation of atopic dermatitis after 5 days of use on the formulation of DERMOTIC OIL.

Evaluation in Pediatric Patients 2 to 6 years old
Use of the formulation of DERMOTIC OIL in pediatric patients 2 to 6 years old is supported by open-label safety trials conducted in 33 pediatric subjects (20 subjects ages 2 to 6 years, 13 subjects ages 7 to 12 years) with moderate to severe stable atopic dermatitis. Baseline body surface area involvement was 50% to 75% in 15 subjects and greater than 75% in 18 subjects. Subjects were treated with the formulation of DERMOTIC OIL twice daily for 4 weeks. Morning pre-stimulation cortisol and post-ACTH stimulation cortisol levels were obtained in each subject the beginning of the trial and at the end of 4 weeks of treatment. At the end of treatment, 4 out of 18 subjects aged 2 to 5 years showed low pre-stimulation cortisol levels (3.2 to 6.6 µg/dL; normal: cortisol > 7µg/dL) but all had normal responses to 0.25 mg of ACTH stimulation (cortisol > 18 µg/dL) [see Clinical Pharmacology (12.2)].

11 DESCRIPTION

DERMOTIC OIL (fluocinolone acetonide) 0.01% ear drops contains fluocinolone acetonide [(6α, 11β, 16α)-6,9-difluoro-11,21-dihydroxy-16, 17[(1-methylethylidene)bis(oxy)]-pregna-1,4-diene3,20-dione, cyclic 16,17 acetal with acetone], a synthetic corticosteroid for topical dermatologic use. Chemically, fluocinolone acetonide is C24H30F2O6. It has the following structural formula:

Fluocinolone acetonide has a molecular weight of 452.50. It is a white crystalline powder that is odorless, stable in light, and melts at 270°C with decomposition; soluble in alcohol, acetone and methanol; slightly soluble in chloroform; insoluble in water.

Each gram of DERMOTIC OIL contains approximately 0.11 mg of fluocinolone acetonide in a blend of oils, which contains isopropyl alcohol, isopropyl myristate, light mineral oil, oleth-2, refined peanut oil and fragrances.

DERMOTIC OIL is formulated with 48% refined peanut oil. The bulk refined peanut oil, used in DERMOTIC OIL is heated at 246°C (475°F) for at least 15 minutes. The refined peanut oil used in DERMOTIC OIL is routinely tested for peanut proteins through amino acid analysis; the quantity of amino acids is below 0.5 parts per million (ppm).

12 CLINICAL PHARMACOLOGY

12.1 Mechanism of Action

Corticosteroids play a role in cellular signaling, immune function, inflammation, and protein regulation; however, the precise mechanism of action in eczematous external otitis is unknown.

12.2 Pharmacodynamics

Vasoconstrictor Assay
DERMOTIC OIL is in the low to medium range of potency as compared with other topical corticosteroids in vasoconstrictor studies. However, similar blanching scores do not necessarily imply therapeutic equivalence.

Hypothalamic-Pituitary-Adrenal (HPA) Axis Suppression
HPA axis suppression was evaluated in 33 pediatric subjects 2 to 12 years old (20 subjects ages 2 to 6 years, 13 subjects ages 7 to 12 years) with moderate to severe stable atopic dermatitis. Subjects were treated with the formulation of DERMOTIC OIL twice daily for 4 weeks. Baseline body surface area involvement was 50% to 75% in 15 subjects and greater than 75% in 18 subjects. Morning pre-stimulation cortisol and post-ACTH stimulation cortisol levels were obtained in each subject at the beginning of the trial and at the end of 4 weeks of treatment. At the end of treatment, 4 out of 18 subjects aged 2 to 5 years showed low pre-stimulation cortisol levels (3.2 to 6.6 µg/dL; normal cortisol >7 µg/dL) but all had normal responses to 0.25 mg of ACTH stimulation (cortisol > 18 µg/dL) [see Warnings and Precautions (5.1)].

12.3 Pharmacokinetics

Topical corticosteroids can be absorbed from intact healthy skin. The extent of percutaneous absorption of topical corticosteroids is determined by many factors, including the product formulation and the integrity of the epidermal barrier. Occlusion, inflammation and/or other disease processes in the skin may increase percutaneous absorption. The use of pharmacodynamic endpoints for assessing the systemic exposure of topical corticosteroids may be necessary due to the fact that circulating levels are often below the level of detection. Once absorbed through the skin, topical corticosteroids are metabolized, primarily in the liver, and are then excreted by the kidneys. Some corticosteroids and their metabolites are also excreted in the bile.

13 NONCLINICAL TOXICOLOGY

13.1 Carcinogenesis, mutagenesis, impairment of fertility

No carcinogenicity, genotoxicity, or fertility studies were conducted with DERMOTIC OIL. However, some corticosteroids are genotoxic in various genotoxicity tests (i.e., the in vitro human peripheral blood lymphocyte chromosome aberration assay with metabolic activation, the in vivo mouse bone marrow micronucleus assay, the Chinese hamster micronucleus test and the in vitro mouse lymphoma gene mutation assay).

14 CLINICAL STUDIES

In two vehicle-controlled trials (Trial 1 and Trial 2), 154 subjects (adults and pediatric subjects 2 years of age and older) with chronic eczematous external otitis were treated with 5 drops per ear of DERMOTIC OIL twice daily for 7 days. Efficacy was assessed on Day 7 by clearance of the signs and symptoms of eczematous external otitis, and the results are presented in the following table:

Table 2: Efficacy Results at Day 7 in Subjects with Chronic Eczematous External Otitis in Trial 1 and 2 [Erythema, scaling, pruritus, erosion/oozing/crusting and debris]
 | DermOtic Oil | Vehicle
Study 1 | 30% (14/47) | 7% (3/46)
Study 2 | 32% (9/28) | 3% (1/30)

16 HOW SUPPLIED / STORAGE AND HANDLING

DERMOTIC OIL (fluocinolone acetonide oil) 0.01% ear drops is supplied in bottles containing 20 mL, (dropper included) (NDC # 68791-103-20).

STORAGE AND HANDLING

Storage: Keep tightly closed. Store at 20°-25°C (68°-77°F); excursions permitted to 15°-30°C (59°-86°F) [see USP Controlled Room Temperature].

Discard DERMOTIC OIL 2 months after initial use.

17 PATIENT COUNSELING INFORMATION

Administration Instructions

Advise patients that DERMOTIC OIL is for otic administration only and not for oral, ophthalmic, or intravaginal use [see Dosage and Administration (2)].

Advise patients to avoid use of DERMOTIC OIL on the face, axillae, or groin unless directed by their healthcare provider [see Dosage and Administration (2)].

Advise patients to discontinue therapy when control of disease is achieved. Instruct patients to contact their healthcare provider if no improvement is seen within 2 weeks [see Dosage and Administration (2)].

Endocrine System Adverse Reactions
Instruct patients not to use other corticosteroid-containing products while using DERMOTIC OIL without first consulting their healthcare provider [see Warnings and Precautions (5.1)].

Ophthalmic Adverse Reactions
Advise patients to avoid contact with the eyes and in case of contact, wash eyes liberally with water. Instruct patients to tell their healthcare provider if they develop any visual symptoms [see Warnings and Precautions (5.3)].

Pregnancy and Lactation
Advise patients to use DERMOTIC OIL on the smallest area of skin and for the shortest duration possible while pregnant or breastfeeding. Advise patients that are breastfeeding not to apply DERMOTIC OIL directly to the nipple and areola to avoid direct infant exposure [See Use in Specific Populations (8.1 and 8.2)].

Manufactured by:
Hill Dermaceuticals, Inc.
Sanford. Florida 32773

For:
Royal Pharmaceutical, Inc.
Wall, NJ 07719

DERMOTIC is a registered trademark of Hill Dermaceuticals, Inc.
© 2024 Hill Dermaceuticals, Inc. All rights reserved.

PRINCIPAL DISPLAY PANEL - 20 mL Label

NDC 68791-103-20

Rx only

DermOtic® Oil

(fluocinolone acetonide oil) 0.01%

Ear Drops

For Otic Use Only

Not for Ophthalmic Use

Net contents: 20 mL

ROYAL PHARMACEUTICALS®